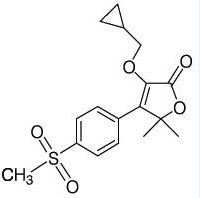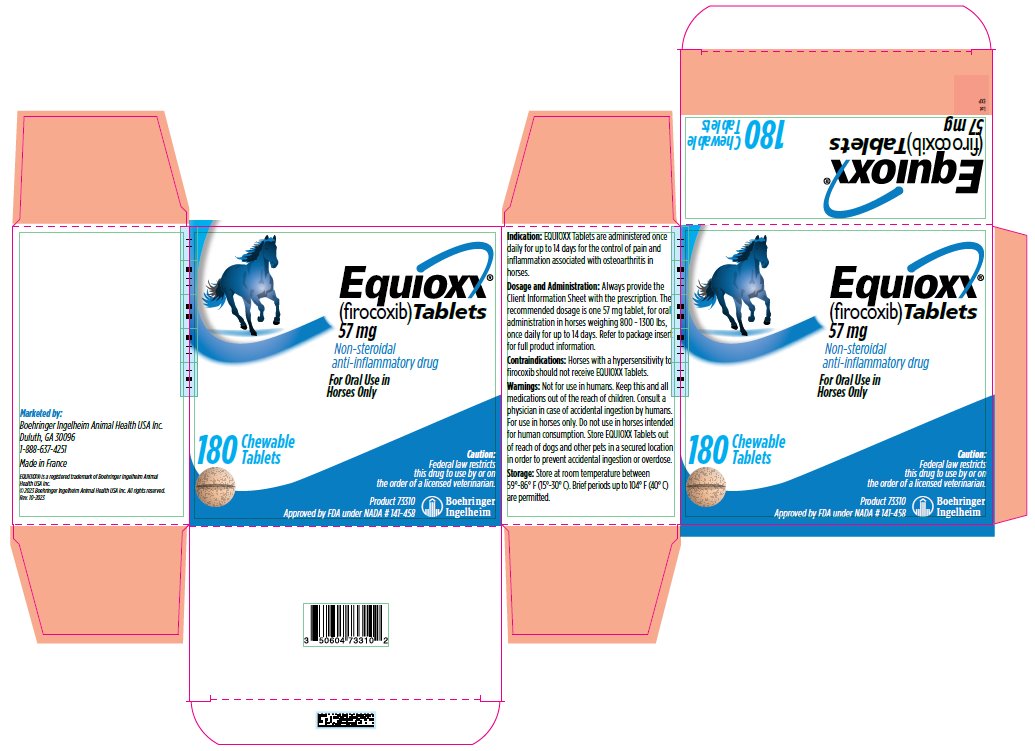 DRUG LABEL: EQUIOXX
NDC: 0010-3309 | Form: TABLET, CHEWABLE
Manufacturer: Boehringer Ingelheim Animal Health USA Inc.
Category: animal | Type: PRESCRIPTION ANIMAL DRUG LABEL
Date: 20240401

ACTIVE INGREDIENTS: firocoxib 57 mg/1 1

Equioxx®
(firocoxib) Tablets
57 mg

CAUTION: Federal (USA) law restricts this drug to use by or on the order of a licensed veterinarian.

Description:

EQUIOXX (firocoxib) Tablets belongs to the coxib class of non-narcotic, non-steroidal anti-inflammatory drugs (NSAIDs). Firocoxib is a white crystalline compound described chemically as 3 (cyclopropylmethoxy)-4-(4-methylsulfonyl)phenyl)-5,5-dimethylfuranone. The empirical formula is C17H20O5S, and the molecular weight is 336.4 g/mol. The structural formula is shown below:

Indications:

EQUIOXX Tablets are administered once daily for up to 14 days for the control of pain and inflammation associated with osteoarthritis in horses.

Dosage and Administration:

Always provide the Client Information Sheet with the prescription. The recommended dosage of EQUIOXX Tablets is one 57 mg tablet administered orally to horses weighing 800 – 1300 lbs, once daily for up to 14 days. For ease of administration, EQUIOXX Tablets may be given with food.

The overall duration of treatment with any firocoxib formulation in horses, including EQUIOXX Tablets, Injection or Oral Paste, should not exceed 14 days. Please see the package insert for EQUIOXX Injection or Oral Paste for appropriate prescribing information for those formulations.

Contraindications:

Horses with a hypersensitivity to firocoxib should not receive EQUIOXX® Tablets.

Warnings:

For use in horses only. Do not use in horses intended for human consumption. Store EQUIOXX Tablets out of the reach of dogs and other pets in a secured location in order to prevent accidental ingestion or overdose.

SAFE HANDLING WARNING

Human Warnings: Not for use in humans. Keep this and all medications out of the reach of children. Consult a physician in case of accidental ingestion by humans.

Precautions:

Horses should undergo a thorough history and physical examination before initiation of NSAID therapy. Appropriate laboratory tests should be conducted to establish hematological and serum biochemical baseline data before and periodically during administration of any NSAID. Clients should be advised to observe for signs of potential drug toxicity and be given a Client Information Sheet with each prescription. See Information for Owner or Person Treating Horse section of this package insert.

Treatment with EQUIOXX Tablets should be terminated if signs such as inappetence, colic, abnormal feces, or lethargy are observed.

As a class, cyclooxygenase inhibitory NSAIDs may be associated with gastrointestinal, renal, and hepatic toxicity. Sensitivity to drug-associated adverse events varies with the individual patient. Horses that have experienced adverse reactions from one NSAID may experience adverse reactions from another NSAID. Patients at greatest risk for adverse events are those that are dehydrated, on diuretic therapy, or those with existing renal, cardiovascular, and/or hepatic dysfunction. Concurrent administration of potentially nephrotoxic drugs should be carefully approached or avoided. NSAIDs may inhibit the prostaglandins that maintain normal homeostatic function. Such anti-prostaglandin effects may result in clinically significant disease in patients with underlying or pre-existing disease that has not been previously diagnosed. Since many NSAIDs possess the potential to produce gastrointestinal ulcerations and/or gastrointestinal perforation, concomitant use of EQUIOXX Tablets with other anti-inflammatory drugs, such as NSAIDs or corticosteroids, should be avoided.

The concomitant use of protein bound drugs with EQUIOXX Tablets has not been studied in horses. The influence of concomitant drugs that may inhibit the metabolism of EQUIOXX Tablets has not been evaluated. Drug compatibility should be monitored in patients requiring adjunctive therapy.

The safe use of EQUIOXX Tablets in horses less than one year in age, horses used for breeding, or in pregnant or lactating mares has not been evaluated.

Consider appropriate washout times when switching from one NSAID to another NSAID or corticosteroid.

Adverse Reactions:

The safety and effectiveness of EQUIOXX Tablets was established in a relative bioavailability study comparing EQUIOXX Tablets and EQUIOXX (firocoxib) Oral Paste. Therefore, additional field studies were not performed to support the effectiveness of EQUIOXX Tablets.

In controlled field studies, 127 horses (ages 3 to 37 years) were evaluated for safety when given EQUIOXX Oral Paste at a dose of 0.045 mg/lb (0.1 mg/kg) orally once daily for up to 14 days. The following adverse reactions were observed. Horses may have experienced more than one of the observed adverse reactions during the study.

Table 1: Adverse Reactions Seen in U.S. Field Studies with EQUIOXX Oral Paste:
Adverse Reactions | EQUIOXX n = 127 | Active Control n = 125
Abdominal pain | 0 | 1
Diarrhea | 2 | 0
Excitation | 1 | 0
Lethargy | 0 | 1
Loose stool | 1 | 0
Polydipsia | 0 | 1
Urticaria | 0 | 1

In these field trials, EQUIOXX Oral Paste was safely used concomitantly with other therapies, including vaccines, anthelmintics, and antibiotics. The safety data sheet (SDS) contains more detailed occupational safety information.

To report suspected adverse events, for technical assistance, or to obtain a copy of the SDS, contact Boehringer Ingelheim Animal Health USA Inc. at 1-888-637-4251. For additional information about adverse drug experience reporting for animal drugs, contact FDA at 1-888-FDA-VETS or online at http://www.fda.gov/AnimalVeterinary/SafetyHealth.

Information for Owner or Person Treating Horse:

A Client Information Sheet should be provided to the person treating the horse. Treatment administrators and caretakers should be aware of the potential for adverse reactions and the clinical signs associated with NSAID intolerance. Adverse reactions may include erosions and ulcers of the gums, tongue, lips and face, weight loss, colic, diarrhea, or icterus. Serious adverse reactions associated with this drug class can occur without warning and, in some situations, result in death. Clients should be advised to discontinue NSAID therapy and contact their veterinarian immediately if any of these signs of intolerance are observed. The majority of patients with drug-related adverse reactions recover when the signs are recognized, drug administration is stopped, and veterinary care is initiated.

Clinical Pharmacology:

Relative Bioavailability Study

A pharmacokinetic study was conducted to compare the relative bioavailability of an oral firocoxib tablet containing 57 mg firocoxib (EQUIOXX Tablets) to the approved paste formulation (EQUIOXX Oral Paste; NADA 141-253). The criteria for the Test/Reference (T/R) ratios and the 90% Confidence Intervals (CI) of EQUIOXX Tablets (test product) were adjusted on the basis of the safety and effectiveness data for EQUIOXX Oral Paste (reference product). The lower bound of the 90% CI for effectiveness was defined by the minimal effective plasma concentration in the study used to support the dosage characterization of EQUIOXX Oral Paste. Effectiveness was based upon the area under the plasma drug concentration-time curve to the last quantifiable concentration (AUClast), with the effectiveness criteria set at a T/R ratio of greater than or equal to 0.77 and a corresponding lower bound for the 90% CI set at 0.71. The upper bound of the 90% CI for safety was defined by the maximum safe plasma concentration (Cmax) in the study used to establish a margin of safety for EQUIOXX Oral Paste Based upon that margin of safety, product safety was defined as a T/R of less than or equal to 1.53, with a corresponding upper bound for the 90% CI of 1.71.

The relative bioavailability study was a randomized, two period, two sequence crossover study in thirty horses. Each horse received a single tablet (57 mg firocoxib) and a single tube of paste (56.7 mg firocoxib). Blood samples were collected at 15 minutes, 45 minutes, 1, 1.5, 2, 3, 4, 6, 8, 12, 24, 32, 48, 72, 96 and 120 hours following each treatment. Samples were analyzed by LC-MS/MS for firocoxib concentrations. The results of the relative bioavailability study are summarized in Table 2. The Cmax and AUClast of EQUIOXX Tablets were within the adjusted 90% CI for safety and effectiveness and met the criteria established for successfully demonstrating that EQUIOXX Tablets will be safe and effective. Therefore, EQUIOXX Tablets and EQUIOXX Oral Paste are acceptable as pharmaceutical alternatives.

There was a substantial difference in the Tmax (time to maximum plasma concentration) between EQUIOXX Oral Paste and EQUIOXX Tablets. The Tmax ranged from 0.25-4 hours for EQUIOXX Oral Paste and 0.25-12 hours for EQUIOXX Tablets. The difference in the rate and extent of absorption was greatest within the first three hours after administration. The mean terminal elimination half-life of EQUIOXX Oral Paste (45.45 hours) was similar to that of EQUIOXX Tablet (44.49 hours).

Table 2: Relative Bioavailability Results for EQUIOXX Oral Paste (Reference) and EQUIOXX Tablets (Test) (n=30 horses)
Parameter | Units | Reference Geometric Mean | Test Geometric Mean | Test/Reference | Lower 90% CI | Upper 90% CI
Cmax | ng/mL | 78.44 | 58.85 | 0.75 | 67.92 | 82.88
AUC last | hr*ng/mL | 2515.77 | 2336.32 | 0.93 | 86.37 | 99.85
Cmax= maximum observed plasma concentration
AUClast = Area Under the Curve to the last quantifiable time point
CI= Confidence Interval

The major metabolism mechanism of firocoxib in the horse is decyclopropylmethylation followed by glucuronidation of that metabolite. Based upon radiolabel studies done for the firocoxib paste formulation, the majority of firocoxib is eliminated in the urine as the decyclopropylmethylated metabolite. Despite a high degree of plasma protein binding (98%), firocoxib exhibits a large volume of distribution (mean Vd(ss) = 1652 mL/kg). The terminal elimination half-life (T1/2) in plasma averages 30-40 hours after IV, oral paste or tablet dosing. Therefore, drug accumulation occurs with repeated dose administrations and steady state concentrations are achieved beyond 6-8 daily oral doses in the horse.

Mode of Action

EQUIOXX (firocoxib) Tablets is a cyclooxygenase-inhibiting (coxib) class, non-narcotic, non-steroidal anti-inflammatory drug (NSAID) with anti-inflammatory, analgesic and antipyretic activity^1 in animal models. Based on in vitro horse data, firocoxib is a selective inhibitor of prostaglandin biosynthesis through inhibition of the inducible cyclooxygenase-2-isoenzyme (COX-2)^2,3. Firocoxib selectivity for the constitutive isoenzyme, cyclooxygenase-1 (COX-1) is relatively low. However, the clinical significance of these in vitro selectivity findings has not been established.

Effectiveness:

The effectiveness of EQUIOXX Tablets was established in a relative bioavailability study comparing EQUIOXX Tablets and EQUIOXX Oral Paste. Therefore, additional field studies were not performed to support the effectiveness of EQUIOXX Tablets. (See CLINICAL PHARMACOLOGY, Relative Bioavailability Study).

Two hundred fifty-three client-owned horses of various breeds, ranging in age from 2 to 37 years and weighing from 595 to 1638 lbs, were randomly administered EQUIOXX Oral Paste or an active control drug in multi-center field studies. Two hundred forty horses were evaluated for effectiveness and 252 horses were evaluated for safety. Horses were assessed for lameness, pain on manipulation, range of motion, joint swelling, and overall clinical improvement in a non-inferiority evaluation of EQUIOXX Oral Paste compared to an active control. At study's end, 84.4% of horses treated with EQUIOXX Oral Paste were judged improved on veterinarians' clinical assessment, and 73.8% were also rated improved by owners. Horses treated with EQUIOXX Oral Paste showed improvement in veterinarian-assessed lameness, pain on manipulation, range of motion, and joint swelling that was comparable to the active control.

Animal Safety:

The safety of EQUIOXX Tablets was supported by a relative bioavailability study comparing EQUIOXX Tablets and EQUIOXX Oral Paste (see CLINICAL PHARMACOLOGY, Relative Bioavailability Study), pharmacovigilance information, and target animal safety data for existing firocoxib containing products in horses. No additional target animal safety studies were conducted with EQUIOXX Tablets.

In a target animal safety study conducted to support the approval of EQUIOXX Oral Paste, firocoxib was administered orally to healthy adult horses (two male castrates and four females per group) at 0, 0.1, 0.3 and 0.5 mg firocoxib/kg body weight (1, 3 and 5X the recommended dose) for 30 days. Administration of firocoxib at 0.3 and 0.5 mg/kg body weight was associated with an increased incidence of oral ulcers as compared to the control group but, no oral ulcers were noted with 0.1 mg/kg. There were no other drug-related adverse findings in this study.

In another target animal safety study, firocoxib was administered orally to healthy adult horses (four males or male castrates and four females per group) at 0, 0.1, 0.3 and 0.5 mg firocoxib/kg body weight (1, 3 and 5X the recommended dose) for 42 days. Administration of firocoxib at 0.1, 0.3 and 0.5 mg/kg body weight was associated with delayed healing of pre-existing oral (lip, tongue, gingival) ulcers. In addition, the incidence of oral ulcers was higher in all treated groups as compared to the control group.

Clinical chemistry and coagulation abnormalities were seen in several horses in the 0.5 mg/kg (5X) group. One 5X male horse developed a mildly elevated BUN and creatinine over the course of the study, prolonged buccal mucosal bleeding time (BMBT), and a dilated pelvis of the right kidney. Another 5X male had a similar mild increase in creatinine during the study but did not have any gross abnormal findings. One female in the 5X group had a prolonged BMBT, bilateral tubulointerstitial nephropathy and bilateral papillary necrosis.

Tubulointerstitial nephropathy occurred in one 3X female, two 3X male horses, and the 5X female horse discussed above with the prolonged BMBT. Papillary necrosis was present in one 1X male horse and the 5X female horse discussed above. Despite the gross and microscopic renal lesions, all of the horses were clinically healthy and had normal hematology, clinical chemistry and urinalysis values.

In another target animal safety study, firocoxib was administered orally to healthy adult horses (three females, two male castrates and one male per group) at 0, 0.25 mg/kg, 0.75 mg/kg and 1.25 mg/kg (2.5, 7.5 and 12.5X the recommended dose of 0.1 mg/kg) for 92 days. An additional group of three females, two male castrates and one male per group, was dosed at 1.25 mg/kg for 92 days but was monitored until Days 147-149. There were treatment-related adverse events in all treated groups. These consisted of ulcers of the lips, gingiva and tongue and erosions of the skin of the mandible and head. Gross and microscopic lesions of the kidneys consistent with tubulointerstitial nephropathy were seen in all treated groups. Papillary necrosis was seen in the 2.5X and 12.5X groups. In addition, several 12.5X horses had elevated liver enzymes (GGT, SDH, AST and ALT). One 2.5X horse had increased urine GGT and urine protein levels which was due to renal hemorrhage and nephropathy. Gastric ulcers of the margo plicatus and glandular area were more prevalent in the 2.5X and 7.5X groups, but not seen in the 12.5X group. The group of horses that were monitored until Days 147-149 showed partial to full recovery from oral and skin ulcers, but no recovery from tubulointerstitial nephropathy.

In a target animal safety study conducted to assess the safety of EQUIOXX Injection followed by EQUIOXX Oral Paste in the horse, thirty-two clinically healthy adult horses received EQUIOXX Injection intravenously once daily for five days at doses of either 0 mg/kg (control group); 0.09 mg/kg (1X); 0.27 mg/kg (3X); or 0.45 mg/kg (5X the recommended dose). This was followed by once daily oral administration of EQUIOXX Oral paste for nine days at doses of either 0 mg/kg (control group); 0.1 mg/kg (1X); 0.3 mg/kg (3X); or 0.5 mg/kg (5X the recommended dose). This sequence (five days of EQUIOXX Injection followed by nine days EQUIOXX Oral Paste, for a total of 14 days) was repeated three times for a total treatment duration of 42 days (3X the recommended treatment duration of 14 days). Two male 5X horses demonstrated a white focus in the renal cortex which correlated with tubulointerstitial nephropathy microscopically. The presence of tubulointerstitial nephropathy was considered treatment-related. One horse from the control group and two horses from the 5X group had injection site swellings during treatment. Injection site changes characterized by inflammatory cell influx and rarely tissue necrosis were seen in all study groups including the control group. There was a dose-dependent increase in the incidence of oral ulcers and erosions. Elevated hepatic enzymes (GGT or AST) were noted in all study groups at one or more time points. One male 5X horse with an elevated GGT value on Day 42 was noted to have tubulointerstitial nephropathy at the time of necropsy. For all horses, these hepatic enzyme elevations generally returned to the reference range by the next time point.

Storage Information:

Store at room temperature, between 59°- 86 ° F (15° - 30° C). Brief periods up to 104° F (40° C) are permitted.

How Supplied:

EQUIOXX is available as round, beige to tan, half-scored tablets, containing 57 mg firocoxib. EQUIOXX Tablets are supplied in 60 and 180 count bottles.

REFERENCES

^1McCann ME, Rickes EL, Hora DF, Cunningham PK et al. In vitro effects and in vivo efficacy of a novel cyclooxygenase-2 inhibitor in cats with lipopolysaccharide-induced pyrexia. Am J Vet Res. 2005 Jul;66 (7):1278-84

^2McCann ME, Anderson DR, Brideau C et al. In vitro activity and in vivo efficacy of a novel COX-2 inhibitor in the horse. Proceedings of the Academy of Veterinary Internal Medicine. 2002. Abstract 114, p.789.

^3Data on file

Approved by FDA under NADA # 141-458
Made in France.
®EQUIOXX is a registered trademark of Boehringer Ingelheim Animal Health USA Inc.
©2019 Boehringer Ingelheim Animal Health USA Inc. All rights reserved.

913141

PATIENT INFORMATION

Equioxx®
(firocoxib) Tablets
57 mg

Non-steroidal Anti-inflammatory drug

Information for Horse Owners

EQUIOXX Tablets are administered once daily for up to 14 days for the control of pain and inflammation associated with osteoarthritis in horses.

This summary contains important information about EQUIOXX Tablets. You should read this information before you start giving your horse EQUIOXX Tablets and review it each time your prescription is refilled. This sheet is provided only as a summary and does not take the place of instructions from your veterinarian. Talk to your veterinarian if you need clarification, have questions, or you want to know more about EQUIOXX Tablets.

What is EQUIOXX Tablets?

EQUIOXX Tablets is a veterinary prescription non-steroidal anti-inflammatory drug (NSAID) of the coxib class used to control pain and inflammation associated with osteoarthritis in horses. Osteoarthritis (OA) is a painful condition caused by progressive "wear and tear" of cartilage and other parts of the joints that may result in the following changes or signs in your horse:

- Limping or lameness.
- Decreased activity or exercise (reluctance to stand, walk, trot or run, or difficulty performing these activities).
- Stiffness or decreased movement of joints.

How to give EQUIOXX Tablets to your horse.

EQUIOXX Tablets should be given according to your veterinarian's instructions. Do not change the way you give EQUIOXX Tablets to your horse without first speaking with your veterinarian. Do not exceed 14 days of treatment.

EQUIOXX Tablets may be given with or without food. Do not give PREVICOX® (firocoxib) Chewable Tablets for Dogs to horses, as overdoses may occur and result in serious side effects.

What kind of results can I expect when my horse is on EQUIOXX Tablets for OA?

While EQUIOXX Tablets are not a cure for osteoarthritis, it can control the pain and inflammation associated with OA and can improve your horse's mobility.

Which horses should not receive EQUIOXX Tablets?

Your horse should not be given EQUIOXX Tablets if he/she:

- Has an allergic reaction to firocoxib, the active ingredient in EQUIOXX Tablets.
- Has previously had an allergic reaction (such as hives, facial or lower limb swelling, or red or itchy skin) to aspirin or other NSAIDs.
- Is presently taking aspirin, phenylbutazone, flunixin meglumine, diclofenac, ketoprofen, or other NSAIDs or corticosteroids.
- The safety of EQUIOXX Tablets has not been determined in horses less than one year of age or in breeding horses, pregnant or lactating mares.

EQUIOXX Tablets should only be given orally to horses.

1. EQUIOXX Tablets is not for use in horses intended for human food consumption.
2. People should not take EQUIOXX Tablets. Keep EQUIOXX Tablets and all medications out of the reach of children. Consult a physician in case of accidental ingestion by humans.
3. Store EQUIOXX Tablets out of reach of dogs and other pets in a secured location in order to prevent accidental ingestion or overdose.

What to tell/ask your veterinarian before giving EQUIOXX Tablets.

Talk to your veterinarian about:

- The signs of OA you have observed in your horse, such as limping or stiffness.
- If any tests, such as X-rays, will be done before EQUIOXX Tablets is prescribed.
- How often your horse may need to be examined by your veterinarian.
- The risks and benefits of using EQUIOXX Tablets.

Tell your veterinarian if your horse has ever had the following medical problems:

- Any side effects from taking EQUIOXX Tablets or other NSAIDs, such as aspirin or phenylbutazone.
- Any kidney disease.
- Any liver disease.
- Any gastrointestinal ulcer

Tell your veterinarian about:

- Other medical problems or allergies that your horse has now, or has had in the past.
- All medicines that you are giving or plan to give to your horse, including those you can get without a prescription and any dietary supplements.

Tell your veterinarian if you plan to breed your horse, or if your mare is pregnant or nursing a foal.

What are the possible side effects that may occur in my horse during EQUIOXX Tablets therapy?

EQUIOXX Tablets, like other NSAIDS, may cause some side effects. Serious side effects associated with NSAID therapy in horses can occur with or without warning. The most common side effects associated with EQUIOXX Tablets therapy involve the tongue, lips and skin of the mouth and face (erosions and ulcers of the mucosa and skin) and the kidney. Gastrointestinal, kidney and liver problems have also been reported with other NSAIDs. Look for the following side effects that may indicate your horse is having a problem with EQUIOXX or may have another medical problem:

- Sores or ulcers on the tongue and inside of mouth.
- Sores, scabs, redness, or rubbing of the facial skin, particularly around the mouth.
- Change in eating or drinking habits (frequency or amount consumed).
- Change in urination habits (frequency or color).
- Yellowing of gums, skin, or whites of the eyes (jaundice).
- Unexpected weight loss.
- Change in behavior (such as increased or decreased activity level).

It is important to stop therapy and contact your veterinarian if you think your horse has a medical problem or side effect while taking EQUIOXX Tablets. If you have additional questions about possible side effects, talk with your veterinarian or call 1-888-637-4251.

Can EQUIOXX Tablets be given with other medications?

EQUIOXX® should not be given with other NSAIDs (for example, aspirin, phenylbutazone, diclofenac, ketoprofen or flunixin) or systemic corticosteroids (for example, prednisone, cortisone, dexamethasone, or triamcinolone).

Tell your veterinarian about all medications that you have given your horse in the past, and any medications you are planning to give with EQUIOXX Tablets. This should include other medicines that you can get without a prescription or any dietary supplements. Your veterinarian may want to check that all of your horse's medicines can be given together.

What do I do in case my horse receives more than the prescribed amount of EQUIOXX Tablets?

- Consult your veterinarian if your horse receives more than the prescribed amount of EQUIOXX Tablets.

What else should I know about EQUIOXX Tablets?

- This sheet provides a summary of information about EQUIOXX Tablets and general information about NSAIDs. If you have any questions or concerns about EQUIOXX Tablets or osteoarthritis pain, talk with your veterinarian.
- As with all prescribed medicines, EQUIOXX Tablets should only be given to the horse for which it is prescribed. It should be given to your horse only for the condition for which it is prescribed, at the labeled dose and duration.
- It is important to periodically discuss your horse's response to EQUIOXX Tablets. Your veterinarian will determine if your horse is responding as expected and if your horse should continue receiving EQUIOXX Tablets.

Rev. 11-2018